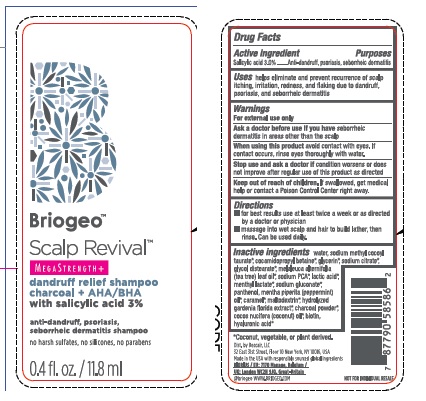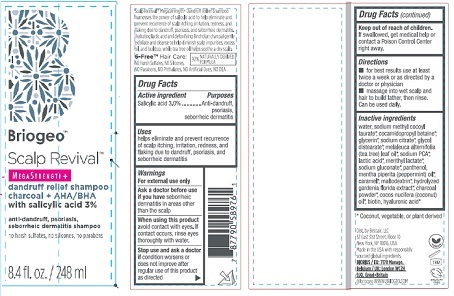 DRUG LABEL: Scalp Revival
NDC: 82594-001 | Form: SHAMPOO
Manufacturer: Beccair, LLC
Category: otc | Type: HUMAN OTC DRUG LABEL
Date: 20250321

ACTIVE INGREDIENTS: SALICYLIC ACID 3.0 g/100 mL
INACTIVE INGREDIENTS: WATER; SODIUM METHYL COCOYL TAURATE; COCAMIDOPROPYL BETAINE; GLYCERIN; SODIUM CITRATE; GLYCOL DISTEARATE; TEA TREE OIL; SODIUM PYRROLIDONE CARBOXYLATE; LACTIC ACID; MENTHYL LACTATE, (-)-; SODIUM GLUCONATE; PANTHENOL; PEPPERMINT OIL; CARAMEL; MALTODEXTRIN; GARDENIA JASMINOIDES FRUIT; ACTIVATED CHARCOAL; COCONUT OIL; BIOTIN; HYALURONIC ACID

Briogeo™ Scalp Revival MegaStrength +

Drug Facts

Active Ingredient

Salicylic Acid 3.0 %

Purposes

Anti-dandruff, psoriasis, seborrheic dermatitis

Uses

helps eliminate and prevent recurrence

of scalp itching, irritation, redness, and

flaking due to dandruff, psoriasis, and

seborrheic dermatitis

Warnings

For external use only

Ask a doctor before use

if you have seborrhic

dermatitis in areas other

than the scalp

When using this product

avoid contact with eyes. If

contact occurs, rinse eyes

thoroughly with water.

Stop use and ask a doctor

if condition worsens or

does not improve after

regular use of tjis product

as directed

Keep out of reach of children.

If swallowed, get medical help or

contact a Poison Control Center

right away.

Directions

■ for best results use at least

twice a week or as directed by a

doctor or physician

■ massage into wet scalp and

hair to build lather, then rinse.

Can be used daily.

Inactive Ingredients

water, sodium methyl cocoyl

taurate*, cocamidopropyl betaine*,

glycerin*, sodium citrate*, glycol

distearate*, melaleuca alternifolia

(tea tree) leaf oil*, sodium PCA*,

lactic acid*, menthyl lactate*,

sodium gluconate*, panthenol,

mentha piperita (peppermint) oil*,

caramel*, maltodextrin*, hydrolyzed

gardenia florida extract*, charcoal

powder*, cocos nucifera (coconut)

oil*, biotin, hyaluronic acid*

* Coconut, vegetable, or plant derived

Product Label

Briogeo™

Scalp Revival

MegaStrength +

8.4 fl. oz./ 248 ml

Dist. by Beccair, LLC

32 East 31st Street, Floor 10

New York, NY 10016, USA

8.4 fl. oz. Bottle

0.4 fl. oz. Packet

res